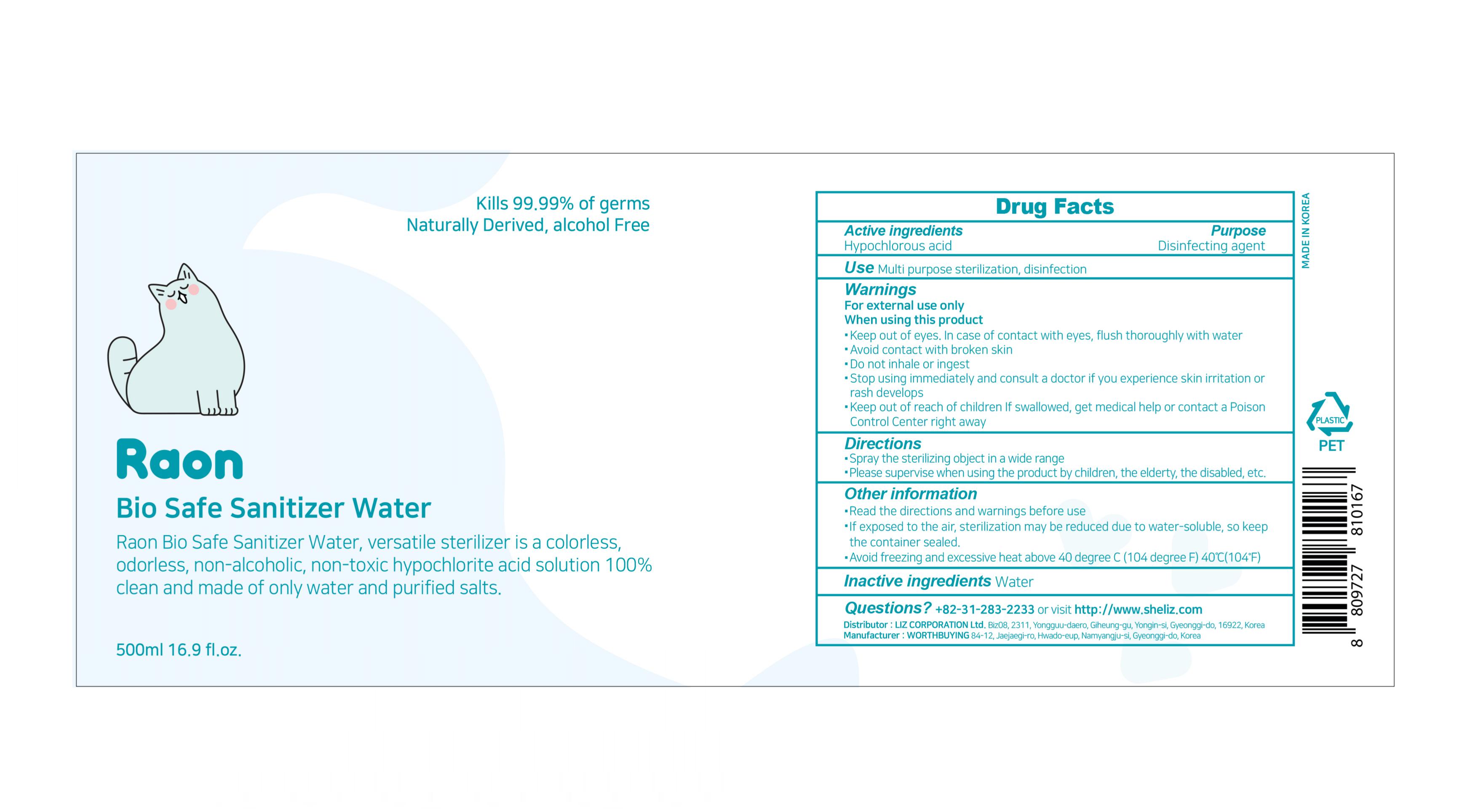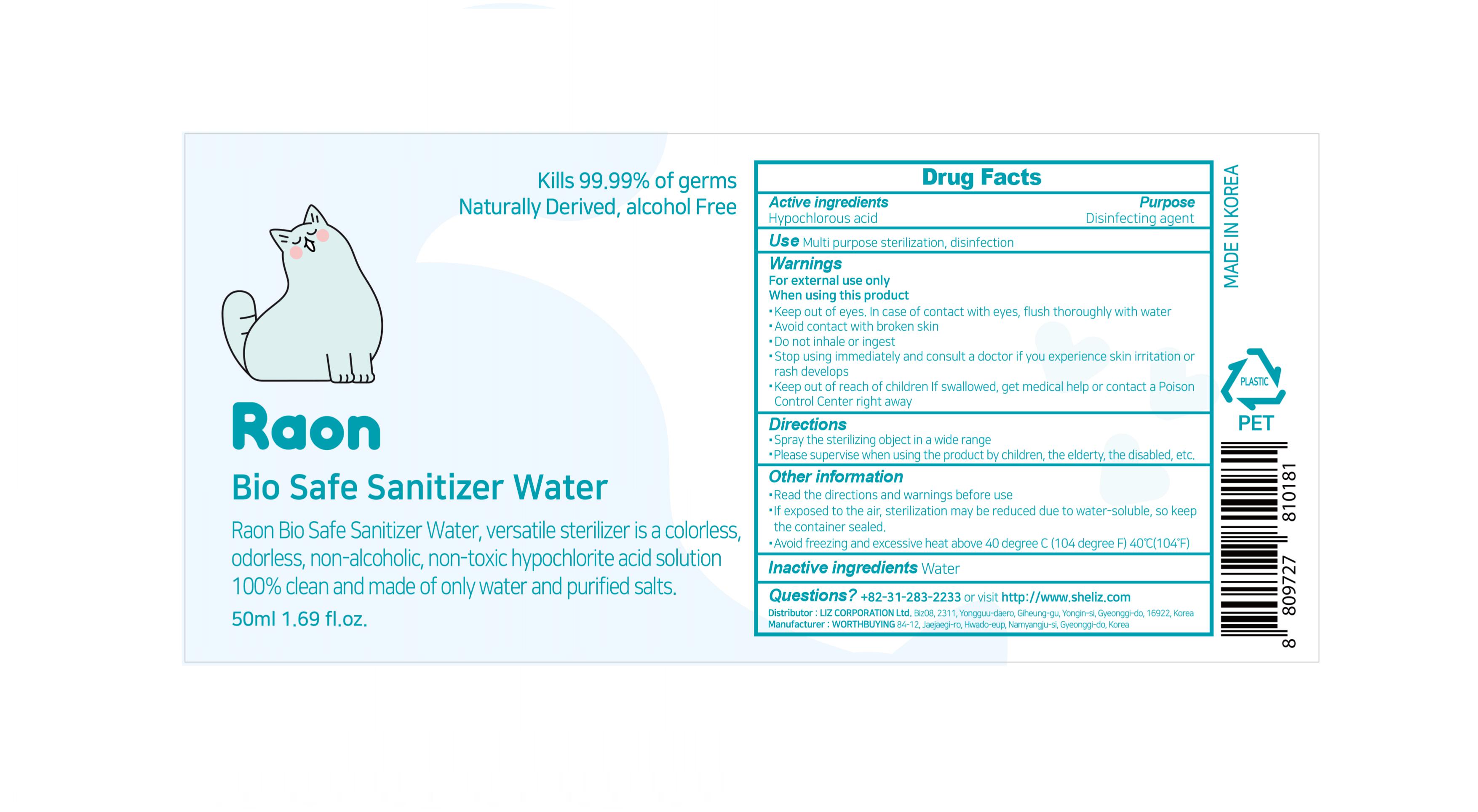 DRUG LABEL: Raon Bio Safe Sanitizer Water
NDC: 79487-201 | Form: LIQUID
Manufacturer: Liz Corporation Co., Ltd
Category: otc | Type: HUMAN OTC DRUG LABEL
Date: 20210708

ACTIVE INGREDIENTS: HYPOCHLOROUS ACID 1 mg/100 mL
INACTIVE INGREDIENTS: WATER

79487-201 Raon Bio Safe Sanitizer Water

Active ingredients

Hypochlorous acid 1%

Purpose

Disinfecting agent

Use

Multi purpose sterilization, disinfection

Warnings

For external use only

When using this product

Keep out of eyes. In case of contact with eyes, flush thoroughly with water

Avoid contact with broken skin

Do not use inhale or ingest

Stop use

Stop using immediately and consult a doctor if you experience skin irritation or rash develops

Keep out of reach of children

If swallowed, get medical help or contact a Poison Control Center right away

Directions

Spray the sterilizing object in a wide range

Please supervise when using the product by children, the elderly, the disabled, etc.

Other information

Read the directions and warnings before use

If exposed to the air, sterilization may be reduced due to water-soluble, so keep the container sealed.

Avoid freezing and excessive heat above 40ºC(104ºF)

Inactive ingredients

Water